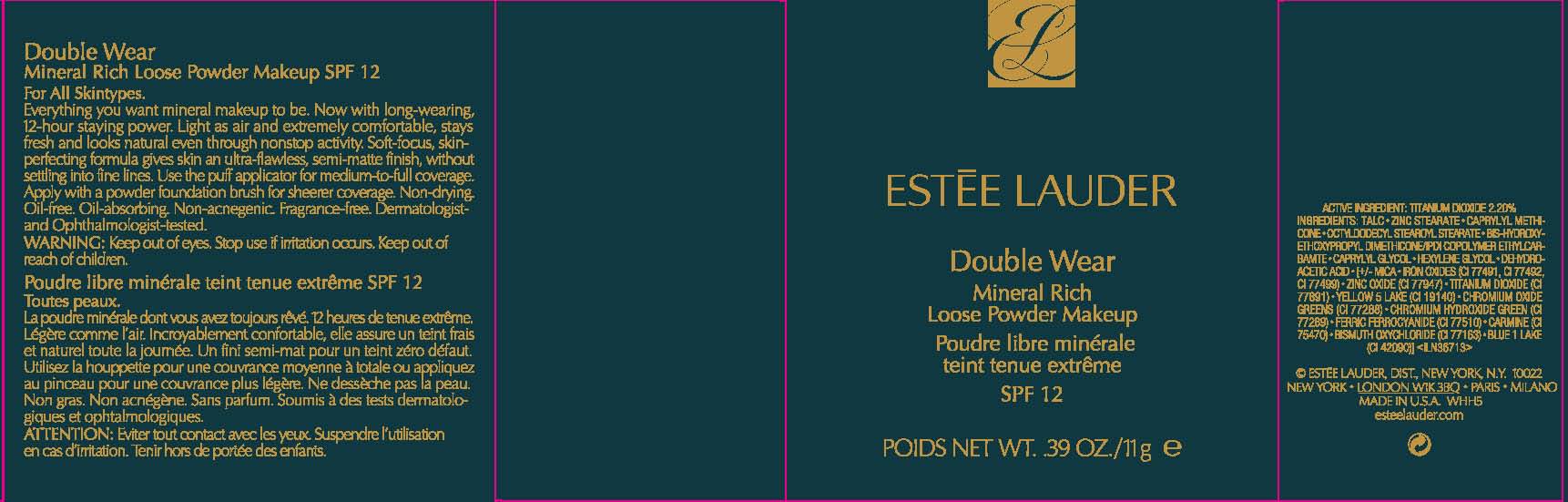 DRUG LABEL: DOUBLE WEAR
NDC: 11559-014 | Form: POWDER
Manufacturer: ESTEE LAUDER INC
Category: otc | Type: HUMAN OTC DRUG LABEL
Date: 20111111

ACTIVE INGREDIENTS: TITANIUM DIOXIDE 2.2 g/100 g
INACTIVE INGREDIENTS: TALC; ZINC STEARATE; OCTYLDODECYL STEAROYL STEARATE; CAPRYLYL GLYCOL; HEXYLENE GLYCOL; DEHYDROACETIC ACID; MICA; ZINC OXIDE; FD&C YELLOW NO. 5; CHROMIC OXIDE; COCHINEAL; FERRIC FERROCYANIDE; BISMUTH OXYCHLORIDE

ACTIVE INGREDIENT: TITANIUM DIOXIDE 2.2%

INACTIVE INGREDIENT

INACTIVE INGREDIENTS: TALC [] ZINC STEARATE [] CAPRYLYL METHICONE [] OCTYLDODECYL STEAROYL STEARATE [] BIS-HYDROXYETHOXYPROPYL DIMETHICONE/IPDI COPOLYMER ETHYLCARBAMTE [] CAPRYLYL GLYCOL [] HEXYLENE GLYCOL [] DEHYDROACETIC ACID [] [+/- MICA [] IRON OXIDES (CI 77491, CI 77492, CI 77499) [] ZINC OXIDE (CI 77947) [] TITANIUM DIOXIDE (CI 77891) [] YELLOW 5 LAKE (CI 19140) [] CHROMIUM OXIDE GREENS (CI 77288) [] CHROMIUM HYDROXIDE GREEN (CI 77289) [] FERRIC FERROCYANIDE (CI 77510) [] CARMINE (CI 75470) [] BISMUTH OXYCHLORIDE (CI 77163) [] BLUE 1 LAKE (CI 42090)]

WARNINGS

WARNING: KEEP OUT OF EYES. STOP USE IF IRRITATION OCCURS. KEEP OUT OF REACH OF CHILDREN.

PACKAGE LABEL

PRINCIPAL DISPLAY PANEL:

ESTEE LAUDER

DOUBLE WEAR

MINERAL RICH LOOSE POWDER MAKEUP

SPF 12

NT WT 0.39 OZ/ 11 g

ESTEE LAUDER DIST

NEW YORK, NY 10022